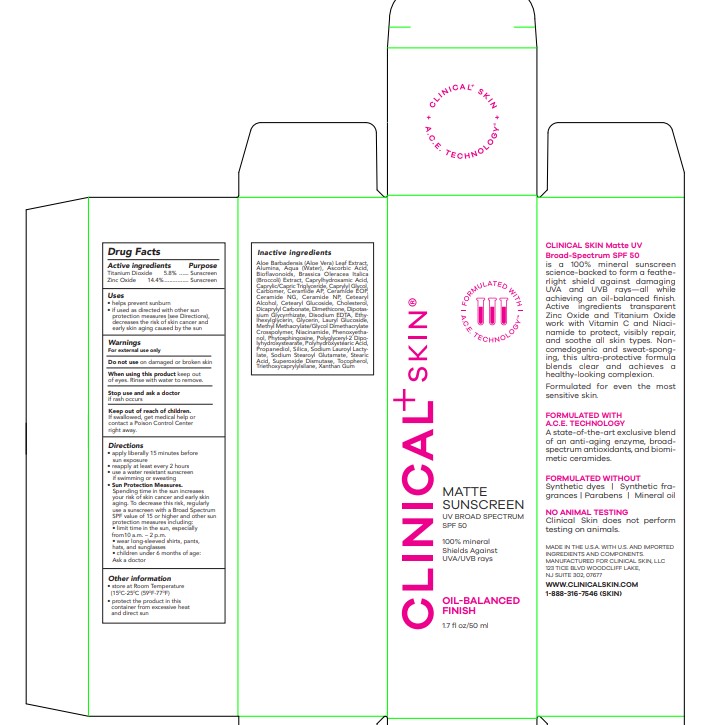 DRUG LABEL: Matte Sunscreen SPF 50
NDC: 84248-025 | Form: LOTION
Manufacturer: CLINICAL SKIN LLC
Category: otc | Type: HUMAN OTC DRUG LABEL
Date: 20240611

ACTIVE INGREDIENTS: ZINC OXIDE 14.4 mg/1 mL; TITANIUM DIOXIDE 5.8 mg/1 mL
INACTIVE INGREDIENTS: BROCCOLI SEED OIL; DIMETHICONE; SILICON DIOXIDE; TOCOPHEROL; ETHYLHEXYLGLYCERIN; PHENOXYETHANOL; LAURYL GLUCOSIDE; SODIUM LAUROYL LACTYLATE; GLYCYRRHIZINATE DIPOTASSIUM; POLYGLYCERYL-2 DIPOLYHYDROXYSTEARATE; METHYL METHACRYLATE/GLYCOL DIMETHACRYLATE CROSSPOLYMER; CAPRYLHYDROXAMIC ACID; GLYCERIN; PHYTOSPHINGOSINE; CAPRYLYL GLYCOL; CERAMIDE NG; CETOSTEARYL ALCOHOL; POLYHYDROXYSTEARIC ACID (2300 MW); ALOE VERA LEAF; WATER; CITRUS BIOFLAVONOIDS; SODIUM STEAROYL GLUTAMATE; EDETATE DISODIUM; CHOLESTEROL; ASCORBIC ACID; ALUMINUM OXIDE; MEDIUM-CHAIN TRIGLYCERIDES; MUSKMELON; NIACINAMIDE; CARBOMER HOMOPOLYMER, UNSPECIFIED TYPE; PROPANEDIOL; STEARIC ACID; TRIETHOXYCAPRYLYLSILANE; XANTHAN GUM; CERAMIDE AP; CERAMIDE NP; DICAPRYLYL CARBONATE; CETEARYL GLUCOSIDE

Clinical Skin Matte Sunscreen SPF 50

Active Ingredients

Titanium Dioxide 5.8%

Zinc Oxide 14.4%

Purpose

Sunscreen

Use

• helps prevent sunburn

• if used as directed with other sun protection measures (see Directions), decreases the risk of skin cancer and early skin aging caused by the sun

Warnings

For external use only

Do not use

on damaged or broken skin

When using this product

keep out of eyes. Rinse with water to remove.

Stop use and ask a doctor

if rash occurs.

Keep out of reach of children.

If swallowed, get medical help or contact a Poison Control Center right away.

Directions

• apply liberally 15 minutes before sun exposure

• reapply at least every 2 hours • use a water resistant sunscreen if swimming or sweating

• Sun Protection Measures. Spending time in the sun increases your risk of skin cancer and early skin aging. To decrease this risk, regularly use a sunscreen with a Broad Spectrum SPF value of 15 or higher and other sun protection measures including:

• limit time in the sun, especially from10 a.m. – 2 p.m.

• wear long-sleeved shirts, pants, hats, and sunglasses

• children under 6 months of age: Ask a doctor

Other Information

• store at Room Temperature (150 C-250 C (590 F-770 F)

• protect the product in this container from excessive heat and direct sun

Inactive ingredients

Aloe Barbadensis (Aloe Vera) Leaf Extract, Alumina, Aqua (Water), Ascorbic Acid, Bioflavonoids, Brassica Oleracea Italica (Broccoli) Extract, Caprylhydroxamic Acid, Caprylic/Capric Triglyceride, Caprylyl Glycol, Carbomer, Ceramide AP, Ceramide EOP, Ceramide NG, Ceramide NP, Cetearyl Alcohol, Cetearyl Glucoside, Cholesterol, Dicaprylyl Carbonate, Dimethicone, Dipotassium Glycyrrhizate, Disodium EDTA, Ethylhexylglycerin, Glycerin, Lauryl Glucoside, Methyl Methacrylate/Glycol Dimethacrylate Crosspolymer, Niacinamide, Phenoxyethanol, Phytosphingosine, Polyglyceryl-2 Dipolyhydroxystearate, Polyhydroxystearic Acid, Propanediol, Silica, Sodium Lauroyl Lactylate, Sodium Stearoyl Glutamate, Stearic Acid, Superoxide Dismutase, Tocopherol, Triethoxycaprylylsilane, Xanthan Gum

PACKAGE LABEL

CLINICAL+ SKIN

MATTE SUNSCREEN

UV BROAD SPECTRUM

SPF 50

100% MINERAL

SHIELDS AGAINST

UVA/UVB RAYS

OIL-BALANCED

FINISH

1.7 FL OZ/50 ML